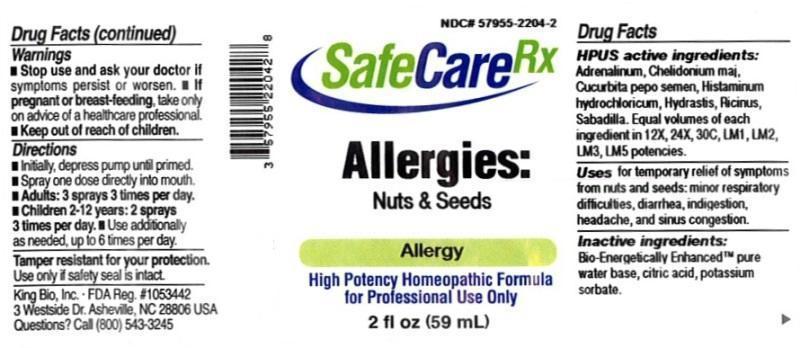 DRUG LABEL: Allergies Nuts and Seeds
NDC: 57955-2204 | Form: LIQUID
Manufacturer: King Bio Inc.
Category: homeopathic | Type: HUMAN OTC DRUG LABEL
Date: 20150728

ACTIVE INGREDIENTS: EPINEPHRINE 12 [hp_X]/12 mL; CHELIDONIUM MAJUS 12 [hp_X]/12 mL; PUMPKIN SEED 12 [hp_X]/12 mL; HISTAMINE DIHYDROCHLORIDE 12 [hp_X]/12 mL; GOLDENSEAL 12 [hp_X]/12 mL; RICINUS COMMUNIS SEED 12 [hp_X]/12 mL; SCHOENOCAULON OFFICINALE SEED 12 [hp_X]/12 mL
INACTIVE INGREDIENTS: WATER; ANHYDROUS CITRIC ACID; POTASSIUM SORBATE

Allergies Nuts and Seeds

ACTIVE INGREDIENT

Drug Facts__________________________________________________________________________________________________________

HPUS active ingredients: Adrenalinum, Chelidonium majus, Cucurbita pepo semen, Histaminum Hydrochloricum, Hydrastis canadensis, Ricinus communis, Sabadilla. Equal volumes of each ingredient in 12X, 24X, 30C, LM1, LM2, LM3, LM5 potencies.

INDICATIONS AND USAGE

Uses for temporary relief of symptoms from nuts and seeds: minor respiratory difficulties, diarrhea, indigestion, headache, and sinus congestion.

Inactive Ingredients:

Bio-Energetically Enhanced™ pure water, citric acid and potassium sorbate.

Warnings

- Stop use and ask your doctor if symptoms persist or worsen.
- If pregnant or breast-feeding, take only on advice of a healthcare professional.

- Keep out of reach of children.

Directions

- Initially, depress pump until primed.
- Spray one dose directly into mouth.
- Adults: 3 sprays 3 times per day.
- Children 2-12 years: 2 sprays 3 times per day.
- Use additionally as needed, up to 6 times per day.

OTHER SAFETY INFORMATION

Tamper resistant for your protection. Use only if seal is intact.

PURPOSE

Uses for temporary relief of symptoms from nuts and seeds:

- minor respiratory difficulties
- diarrhea
- indigestion
- headache
- sinus congestion